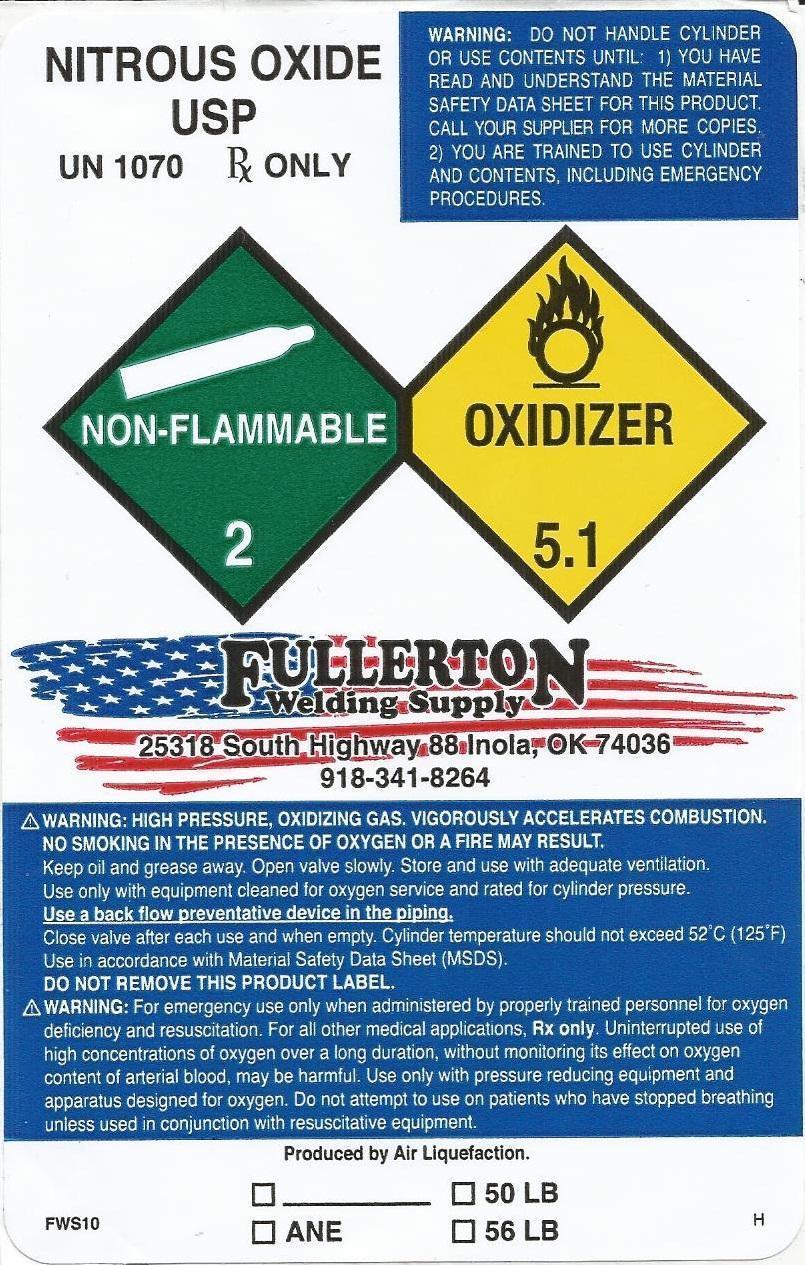 DRUG LABEL: Nitrous Oxide
NDC: 42751-1070 | Form: GAS
Manufacturer: Fullerton Welding Supply
Category: prescription | Type: HUMAN PRESCRIPTION DRUG LABEL
Date: 20130118

ACTIVE INGREDIENTS: NITROUS OXIDE 99 L/100 L

Nitrous Oxide